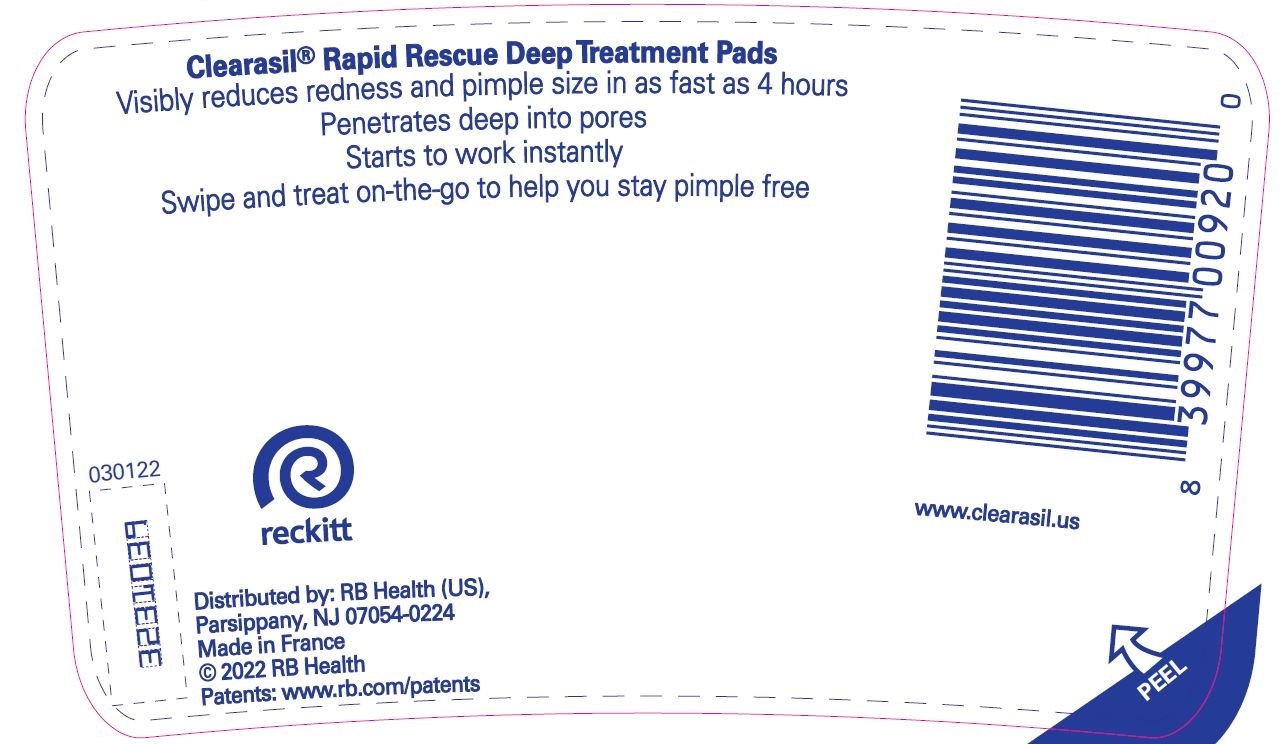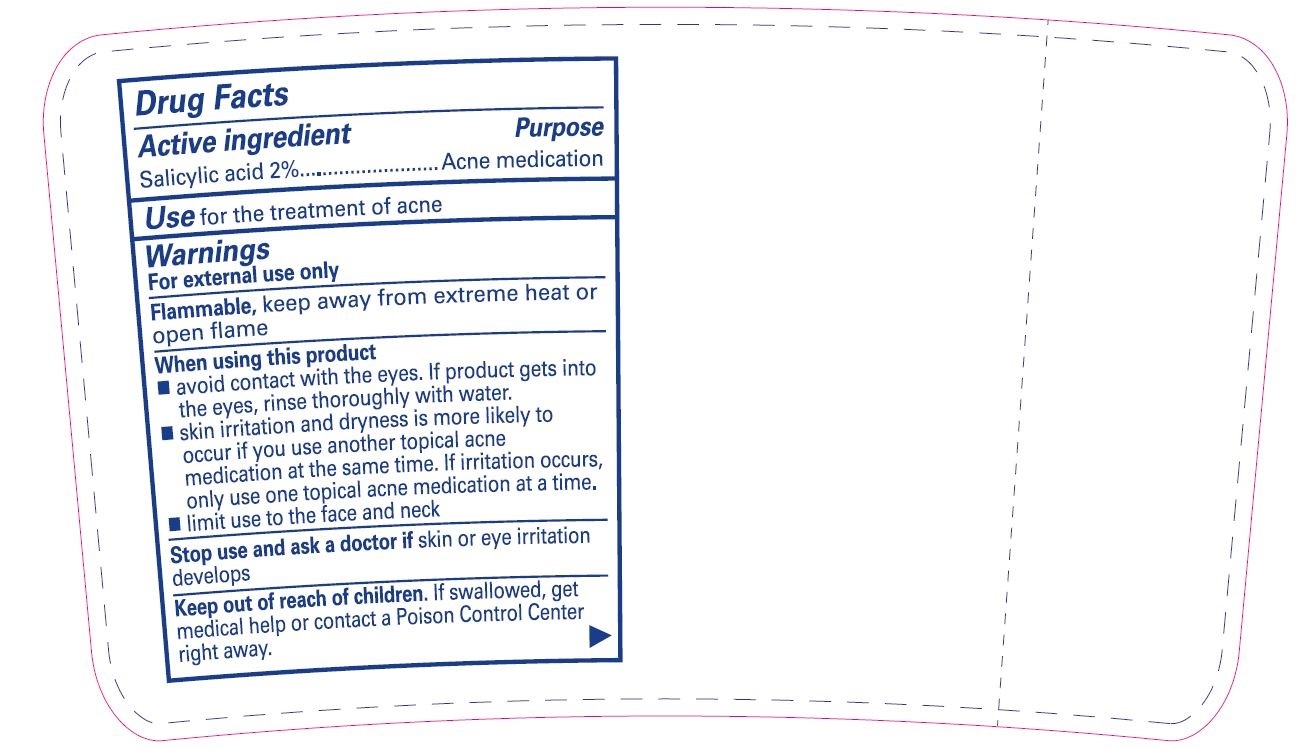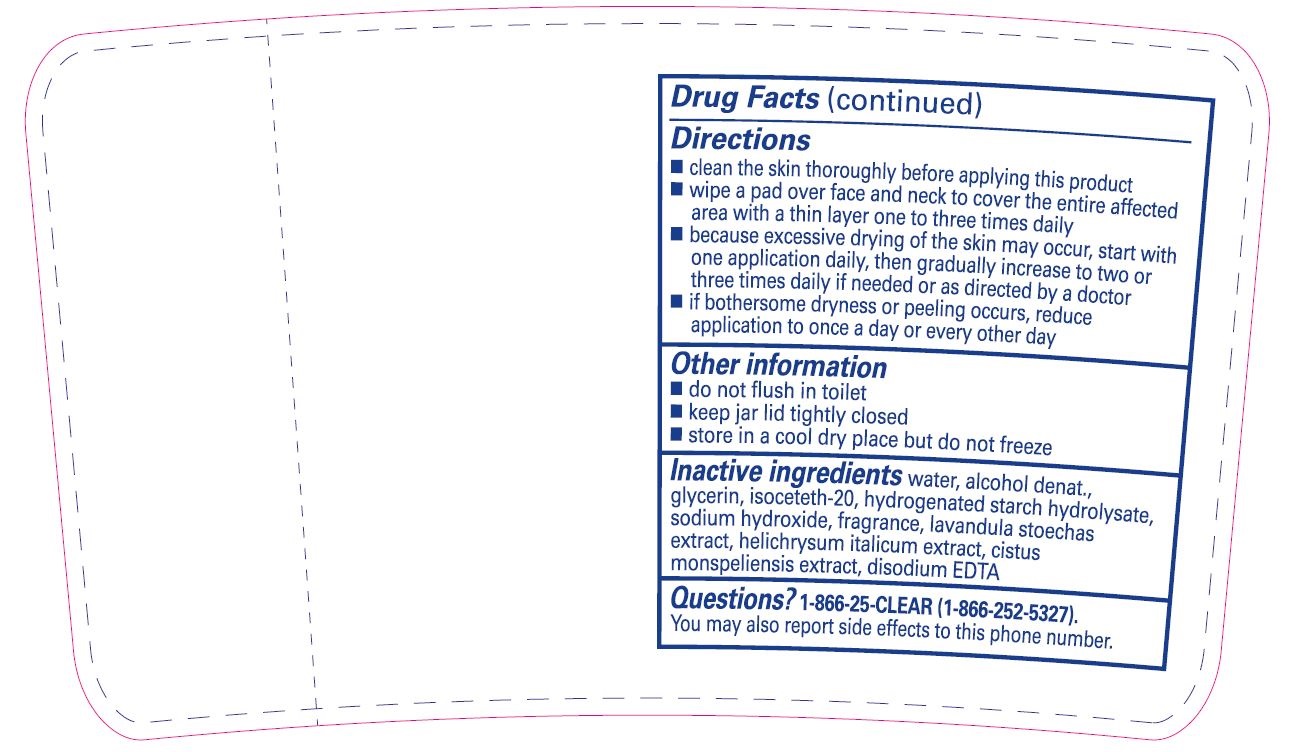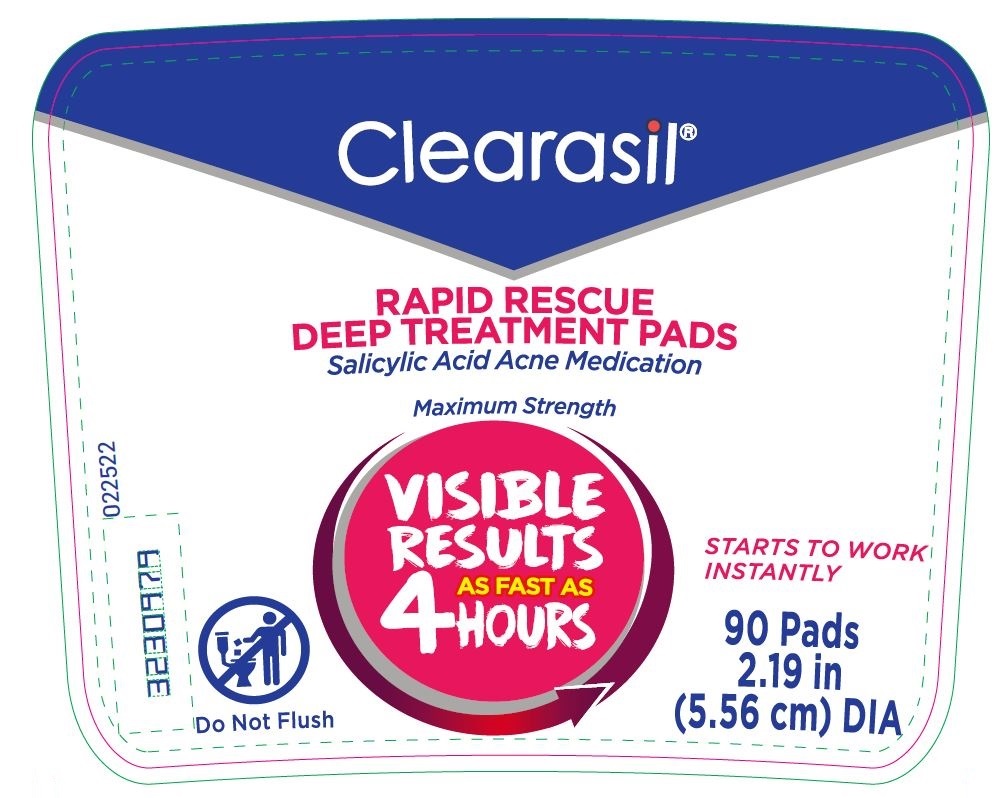 DRUG LABEL: Clearasil Rapid Rescue Deep Treatment Pads
NDC: 63824-431 | Form: CLOTH
Manufacturer: RB Health (US) LLC
Category: otc | Type: HUMAN OTC DRUG LABEL
Date: 20241218

ACTIVE INGREDIENTS: SALICYLIC ACID 0.02 g/1 1
INACTIVE INGREDIENTS: WATER; ALCOHOL; GLYCERIN; ISOCETETH-20; HYDROGENATED STARCH HYDROLYSATE; SODIUM HYDROXIDE; HELICHRYSUM ITALICUM FLOWER; EDETATE DISODIUM ANHYDROUS

Clearasil®Rapid Rescue Deep Treatment Pads

Drug Facts

Active ingredient

Salicylic acid 2%

Purpose

Acne medication

Use

for the treatment of acne

Warnings

For external use only

Flammable,keep away from extreme heat or open flame

When using this product

- avoid contact with the eyes. If product gets into the eyes, rinse thoroughly with water.
- skin irritation and dryness is more likely to occur if you use another topical acne medication at the same time. If irritation occurs, only use one topical acne medication at a time.
- limit use to the face and neck

Stop use and ask a doctor ifskin or eye irritation develops

Keep out of reach of children.If swallowed, get medical help or contact a Poison Control Center right away.

Directions

- clean the skin thoroughly before applying this product
- wipe a pad over face and neck to cover the entire affected area with a thin layer one to three times daily
- because excessive drying of the skin may occur, start with one application daily, then gradually increase to two or three times daily if needed or as directed by a doctor
- if bothersome dryness or peeling occurs, reduce application to once a day or every other day

Other information

- do not flush in toilet
- keep jar lid tightly closed
- store in a cool dry place but do not freeze

Inactive ingredients

Water, Alcohol Denat., Glycerin, Isoceteth-20, Hydrogenated Starch Hydrolysate, Sodium Hydroxide, Fragrance, Lavandula Stoechas Extract, Helichrysum Italicum Extract, Cistus Monspeliensis Extract, Disodium EDTA

Questions?

1-866-25-CLEAR (1-866-252-5327).

You may also report side effects to this phone number.

Distributed by: RB Health (US),
Parsippany, NJ 07054-0224
Made in France

PRINCIPAL DISPLAY PANEL - 90 Pad Jar Label

Clearasil®

RAPID RESCUE
DEEP TREATMENT PADS
Salicylic Acid Acne Medication

Maximum Strength

VISIBLE
RESULTS
AS FAST AS
4 HOURS

STARTS TO WORK
INSTANTLY

90 Pads
2.19 in
(5.56 cm) DIA

080917